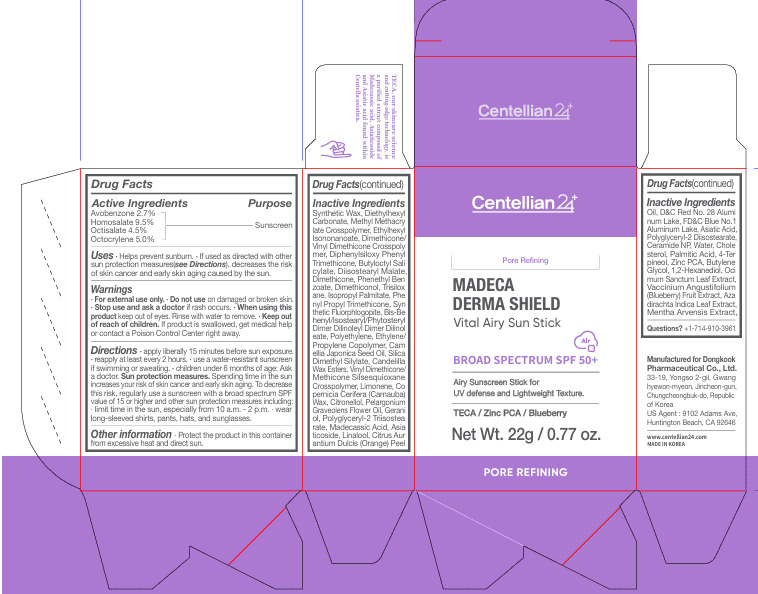 DRUG LABEL: Centellian24 Madeca Derma Shield Vital Airy Sun Stick
NDC: 70541-211 | Form: STICK
Manufacturer: 70541
Category: otc | Type: HUMAN OTC DRUG LABEL
Date: 20260127

ACTIVE INGREDIENTS: OCTISALATE 4.5 g/100 g; OCTOCRYLENE 5 g/100 g; HOMOSALATE 9.5 g/100 g; AVOBENZONE 2.7 g/100 g
INACTIVE INGREDIENTS: WATER

Dosage and administration

Directions · apply liberally 15 minutes before sun exposure. · reapply at least every 2 hours. · use a water-resistant sunscreen if swimming or sweating. · children under 6 months of age: Ask a doctor. Sun protection measures. Spending time in the sun increases your risk of skin cancer and early skin aging. To decrease this risk, regularly use a sunscreen with a broad spectrum SPF value of 15 or higher and other sun protection measures including: · limit time in the sun, especially from 10 a.m. – 2 p.m. · wear long-sleeved shirts, pants, hats, and sunglasses.

Warnings

· For external use only. · Do not use on damaged or broken skin. · Stop use and ask a doctor if rash occurs. · When using this product keep out of eyes. Rinse with water to remove. · Keep out of reach of children. If product is swallowed, get medical help or contact a Poison Control Center right away.

Inactive Ingredients
Synthetic Wax, Diethylhexyl Carbonate, Methyl Methacrylate Crosspolymer, Ethylhexyl Isononanoate, Dimethicone/Vinyl Dimethicone Crosspolymer, Butyloctyl Salicylate, Diphenylsiloxy Phenyl Trimethicone, Diisostearyl Malate, Dimethicone, Phenethyl Benzoate, Dimethiconol, Trisiloxane, Isopropyl Palmitate, Phenyl Propyl Trimethicone, Synthetic Fluorphlogopite, Bis-Behenyl/Isostearyl/Phytosteryl Dimer Dilinoleyl Dimer Dilinoleate, Polyethylene, Ethylene/Propylene Copolymer, Camellia Japonica Seed Oil, Silica Dimethyl Silylate, Candelilla Wax Esters, Vinyl Dimethicone/Methicone Silsesquioxane Crosspolymer, Limonene, Ultramarines (CI 77007), Copernicia Cerifera (Carnauba) Wax, Citronellol, Octyldodecanol, Pelargonium Graveolens Flower Oil, Geraniol, Asiaticoside, Madecassic Acid, Linalool, Citrus Aurantium Dulcis (Orange) Peel Oil, Asiatic Acid, Triethoxycaprylylsilane, Polyhydroxystearic Acid, Neopentyl Glycol Diethylhexanoate, Ceramide NP, Water, Cholesterol, Palmitic Acid, 4-Terpineol, Zinc PCA, Butylene Glycol, 1,2-Hexanediol, Ocimum Sanctum Leaf Extract, Vaccinium Angustifolium (Blueberry) Fruit Extract, Azadirachta Indica Leaf Extract, Mentha Arvensis Extract, Phenoxyethanol

Uses

Uses · Helps prevent sunburn. · If used as directed with other sun protection measures (see Directions), decreases the risk of skin cancer and early skin aging caused by the sun.

Keep out of reach of children. If product is swallowed, get medical help or contact a Poison Control Center right away.

Purpose

Sunscreen